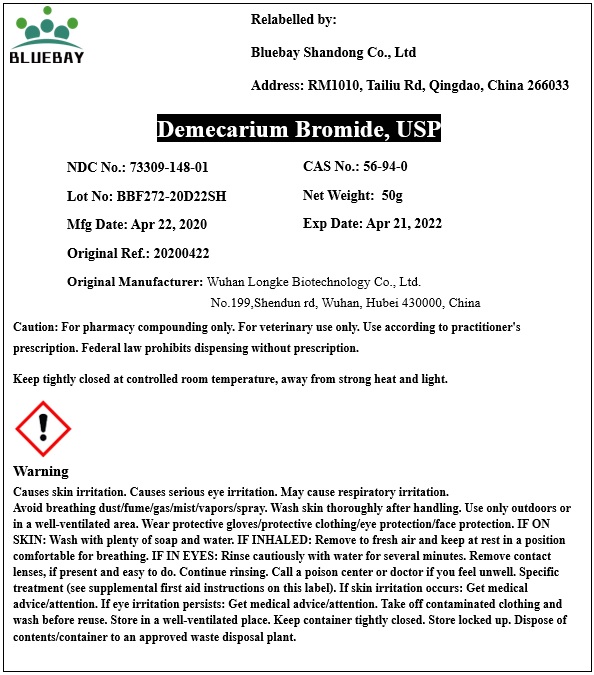 DRUG LABEL: Demecarium Bromide
NDC: 73309-148 | Form: POWDER
Manufacturer: BLUEBAY SHANDONG CO.,LTD
Category: other | Type: BULK INGREDIENT
Date: 20200618

ACTIVE INGREDIENTS: DEMECARIUM BROMIDE 1 g/1 g

Demecarium Bromide